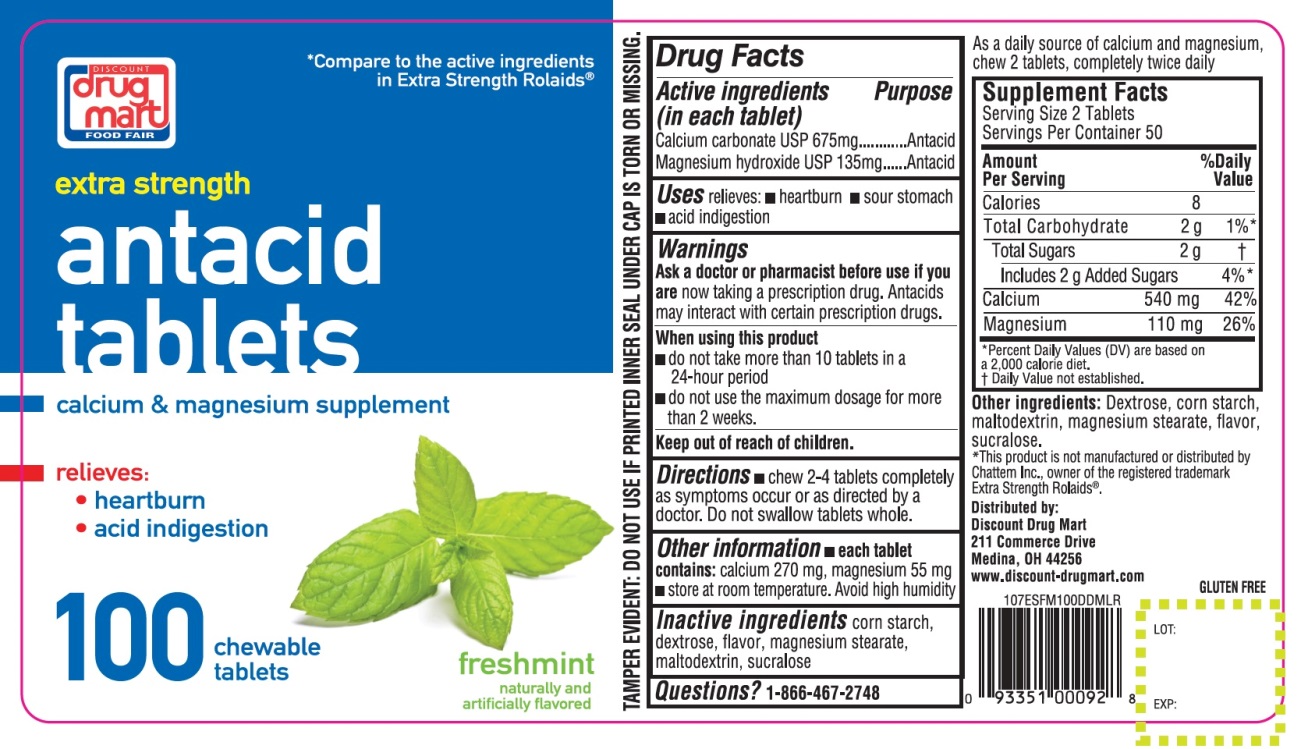 DRUG LABEL: Extra Strength Antacid

NDC: 53943-108 | Form: TABLET, CHEWABLE
Manufacturer: DISCOUNT DRUG MART
Category: otc | Type: HUMAN OTC DRUG LABEL
Date: 20250911

ACTIVE INGREDIENTS: CALCIUM CARBONATE 675 mg/1 1; MAGNESIUM HYDROXIDE 135 mg/1 1
INACTIVE INGREDIENTS: STARCH, CORN; DEXTROSE, UNSPECIFIED FORM; MAGNESIUM STEARATE; MALTODEXTRIN; SUCRALOSE

Drug Mart Extra Strength Antacid Tablets Freshmint Flavor

Drug Facts

Active ingredients(in each tablet)

Calcium Carbonate USP 675 mg
Magnesium hydroxide USP 135 mg

Purpose

Antacid

Antacid

Uses

relieves:

- heartburn
- sour stomach
- acid indigestion
- upset stomach due to these symptoms

Warnings

Ask a doctor or pharmacist before use if you are

presently taking a prescription drug. Antacids may interact with certain prescription drugs.

When using this product

- do not take more than 10 tablets in a 24-hour period
- do not use the maximum dosage for more than 2 weeks

Directions

- chew 2-4 tablets completely as symptoms occur or as directed by a doctor. Do not swallow tablets whole.

Other information

- each tablet contains:calcium 270 mg, magnesium 55 mg
- store at room temperature. Avoid high humidity.

CALCIUM SUPPLEMENT

USES

As a daily source of extra calcium and magnesium chew 2 tablets, completely twice daily.

Supplement Facts

Serving Size: 2 Tablets

Servings Per Container: 50

Amount Per Serving | % Daily Value
Calories 8
Total Carbohydrate 2g | 1%
Total Sugars 2g; Includes 2 g Added Sugars | †; 4%
Calcium 540 mg | 42%
Magnesium 110 mg | 26%

Inactive ingredients

corn starch, dextrose, flavor, magnesium stearate, maltodextrin, sucralose.

Questions?

1-866-467-2748

PRINCIPAL DISPLAY PANEL

DISCOUNT drug mart

FOOD FAIR

NDC# 53943-108-10

Compare to the active ingredients Extra Strength Rolaids®

Extra Strength

Antacid Tablets

Calcium & magnesium Supplement

Relieves:

- Heartburn
- Acid Indigestion

100 CHEWABLE TABLETS

Freshmint

Naturally and artificially flavored

GLUTEN-FREE

TAMPER EVIDENT: DO NOT USE IF PRINTED INNER SEAL UNDER CAP IS TORN OR MISSING.

*This product is not manufactured or distributed by Chattem Inc., owner of the registered trademark Extra Strength Rolaids®

Distributed By:

Drug Mart-Food Fair

211 Commerce Dr., Medina, Ohio 44256

www.discount-drugmart.com

Questions?: 866-467-2748